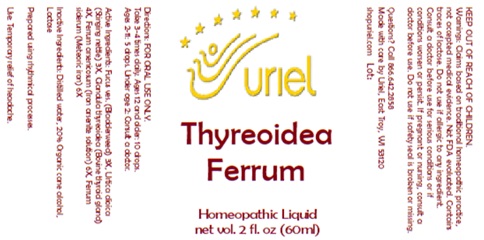 DRUG LABEL: Thyreoidea Ferrum
NDC: 48951-9390 | Form: LIQUID
Manufacturer: Uriel Pharmacy, Inc
Category: homeopathic | Type: HUMAN OTC DRUG LABEL
Date: 20250311

ACTIVE INGREDIENTS: FUCUS VESICULOSUS 3 [hp_X]/1 mL; IRON 6 [hp_X]/1 mL; URTICA DIOICA 3 [hp_X]/1 mL; THYROID, UNSPECIFIED 4 [hp_X]/1 mL; FERROUS ARSENATE 6 [hp_X]/1 mL
INACTIVE INGREDIENTS: WATER; ALCOHOL; LACTOSE

Thyreoidea Ferrum

INDICATIONS AND USAGE

Directions: FOR ORAL USE ONLY.

DOSAGE AND ADMINISTRATION

Take 3-4 times daily. Ages 12 and older: 10 drops.
Ages 2-11: 5 drops. Under age 2: Consult a doctor.

ACTIVE INGREDIENT

Active Ingredients: Fucus ves. (Bladderweed) 3X, Urtica dioica (Stinging nettle) 3X, Glandula thyreoidea (Bovine thyroid gland) 4X, Ferrum arsenicosum (Iron arsenite solution) 6X, Ferrum siderum (Meteoric iron) 6X

INACTIVE INGREDIENT

Inactive Ingredients: Distilled water, 20% Organic cane alcohol, Lactose

Prepared using rhythmical processes.

PURPOSE

Use: Temporary relief of headache.

KEEP OUT OF REACH OF CHILDREN.

WARNINGS

Warnings: Claims based on traditional homeopathic practice, not accepted medical evidence. Not FDA evaluated. Contains traces of lactose. Do not use if allergic to any ingredient. Consult a doctor before use for serious conditions or if conditions worsen or persist. If pregnant or nursing, consult a doctor before use. Do not use if safety seal is broken or missing.

Questions? Call 866.642.2858
Made with care by Uriel, East Troy, WI 53120
shopuriel.com Lot: